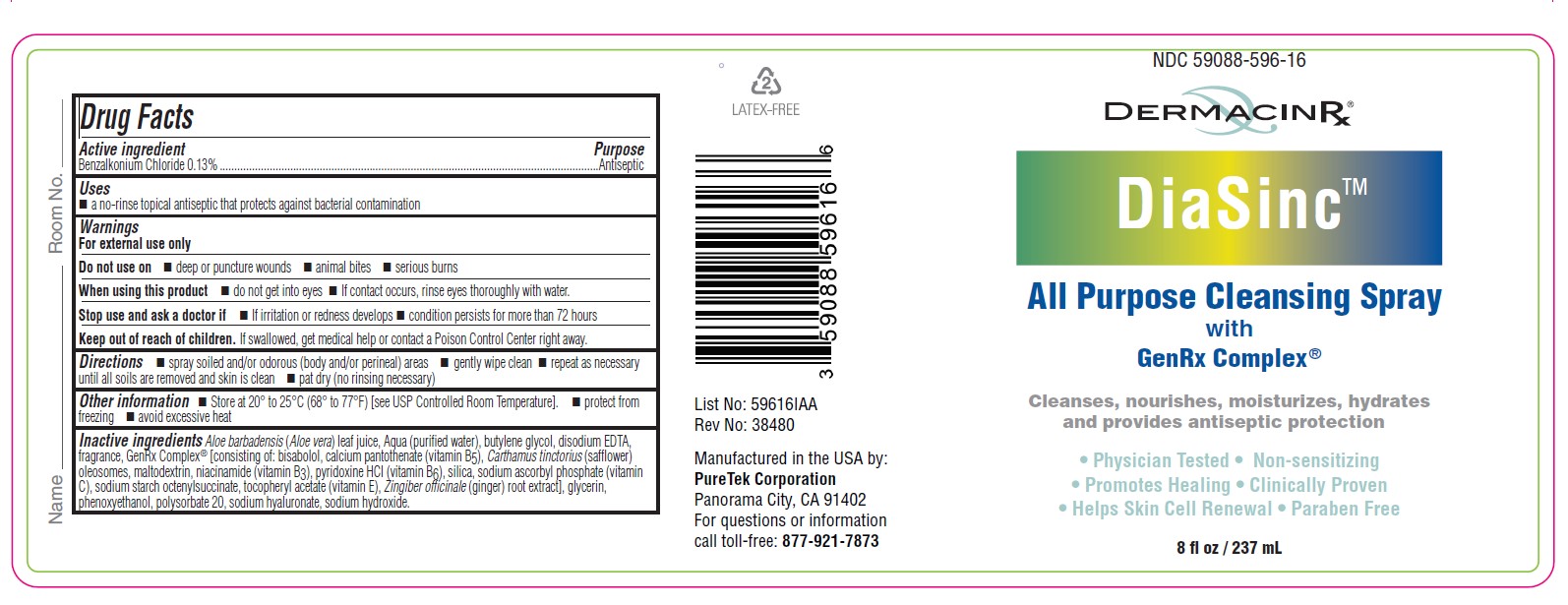 DRUG LABEL: DiaSinc
NDC: 59088-596 | Form: SPRAY
Manufacturer: PureTek Corporation
Category: otc | Type: HUMAN OTC DRUG LABEL
Date: 20241002

ACTIVE INGREDIENTS: BENZALKONIUM CHLORIDE 1.3 mg/1 mL
INACTIVE INGREDIENTS: ALUMINUM STARCH OCTENYLSUCCINATE; ALOE VERA LEAF; BUTYLENE GLYCOL; CALCIUM PANTOTHENATE; EDETATE DISODIUM; GLYCERIN; LEVOMENOL; CARTHAMUS TINCTORIUS SEED OLEOSOMES; MALTODEXTRIN; NIACINAMIDE; PYRIDOXINE HYDROCHLORIDE; SILICON DIOXIDE; SODIUM ASCORBYL PHOSPHATE; ALPHA-TOCOPHEROL ACETATE; GINGER; PHENOXYETHANOL; POLYSORBATE 20; WATER; HYALURONATE SODIUM; SODIUM HYDROXIDE

DiaSinc

Active ingredient

Benzalkonium Chloride 0.13%

Purpose

Antiseptic

Uses

■ a no-rinse topical antiseptic that protects against bacterial contamination

Warnings

For external use only

Do not use on

■ deep or puncture wounds ■ animal bites ■ serious burns

When using this product

■ do not get into eyes ■ If contact occurs, rinse eyes thoroughly with water.

Stop use and ask a doctor if

■ If irritation or redness develops ■ condition persists for more than 72 hours

Keep out of reach of children.

If swallowed, get medical help or contact a Poison Control Center right away.

Directions

■ spray soiled and/or odorous (body and/or perineal) areas ■ gently wipe clean ■ repeat as necessary until all soils are removed and skin is clean ■ pat dry (no rinsing necessary)

Other information

■ Store at 20° to 25°C (68° to 77°F) [see USP Controlled Room Temperature]. ■ protect from freezing ■ avoid excessive heat

Inactive ingredients

aloe barbadensis (aloe vera) leaf juice, aqua (purified water), butylene glycol, disodium EDTA, fragrance, GenRx Complex® [consisting of: bisabolol, calcium pantothenate (vitamin B5), Carthamus tinctorius (safflower) oleosomes, maltodextrin, niacinamide (vitamin B3), pyridoxine HCl (vitamin B6), silica, sodium ascorbyl phosphate (vitamin C), sodium starch octenylsuccinate, tocopheryl acetate (vitamin E), Zingiber officinale (ginger) root extract], glycerin, phenoxyethanol, polysorbate 20, sodium hyaluronate, sodium hydroxide.